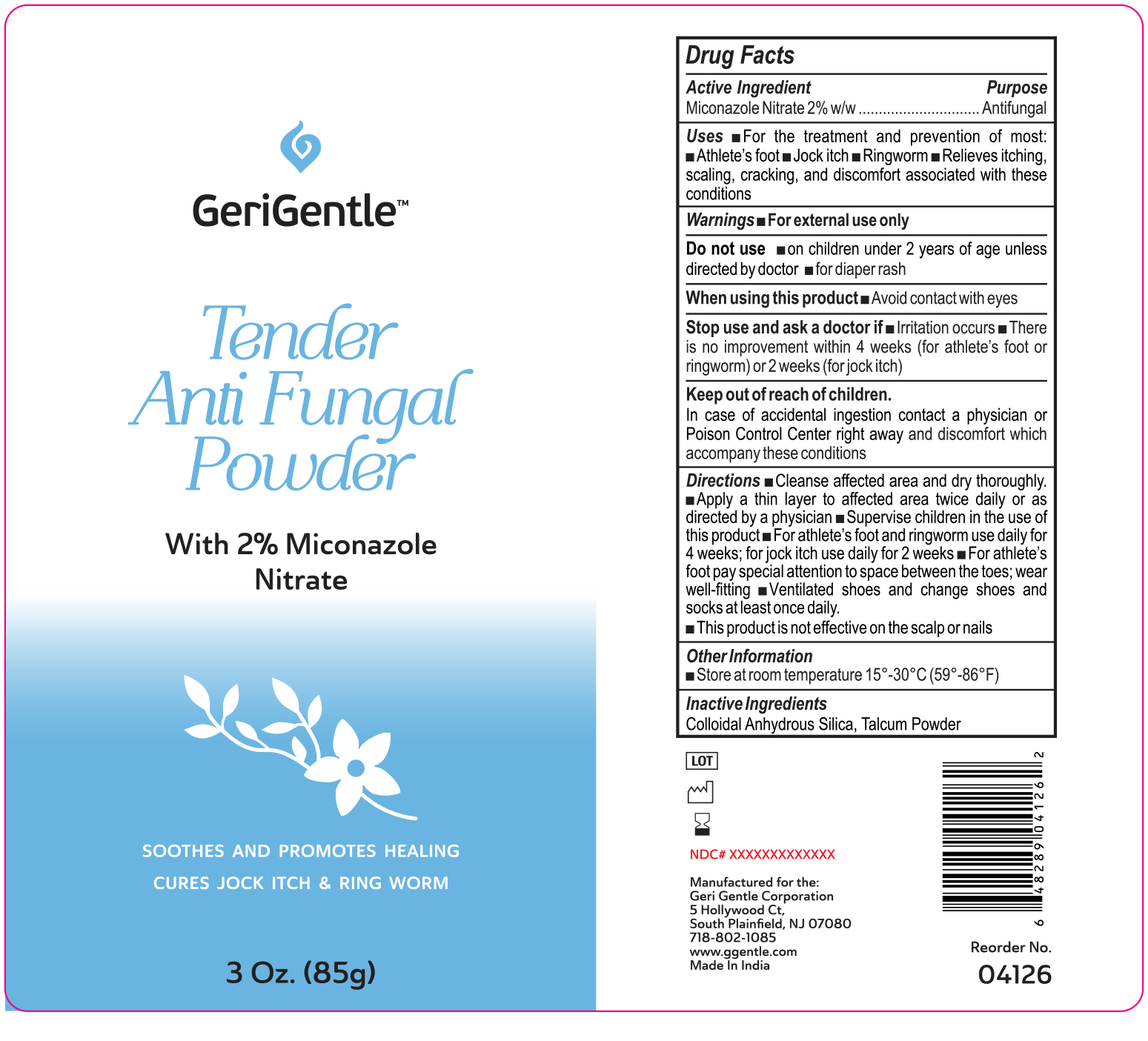 DRUG LABEL: GeriGentle Miconazole nitrate
NDC: 69771-165 | Form: POWDER
Manufacturer: GERI-GENTLE CORPORATION
Category: otc | Type: HUMAN OTC DRUG LABEL
Date: 20251027

ACTIVE INGREDIENTS: MICONAZOLE NITRATE 2 g/100 g
INACTIVE INGREDIENTS: SILICON DIOXIDE; TALC

GeriGentle Miconazole Nitrate Anti-Fungal Powder Talc

Active Ingredients

Miconazole nitrate 2%

Purpose

Antifungal

Uses

fFor the treatment of most athlete’s foot (tinea pedis), jock itch (tinea cruris), ringworm (tinea corporis) ■Relieves itching, scaling, cracking, burning, redness, soreness, irritation, discomfort and chaﬁng associated with jock itch or itching, burning feet

Warnings

For external use only.

Do not use

: ■On children under 2 years of age unless directed by a doctor ■For diaper rash

When using this product

avoid contact with the eyes

Stop use and ask a doctor if

■Irritation occurs

■There is no improvement within 2 weeks when used for the treatment of jock itch ■There is no improvement within 4 weeks when used for athlete's foot or ringworm

Keep out of reach of children.

If swallowed, get medical help or contact a Poison Control Center right away.

Directions

- clean the affected area & dry thoroughly
- apply a thin layer of the product over affected area twice daily (morning and night) or as directed by a doctor
- supervise children in the use of this product
- for athlete's foot: pay special attention to spaces between the toes; wear well-fitting, ventilated shoes, & change shoes & socks at least once daily
- for athlete's foot & ringworm, use daily for 4 weeks; for jock itch, use daily for 2 weeks
- if condition persists longer, consult a doctor
- this product is not effective on the scalp or nails

Other information

- Store at room temperature

Inactive ingredients

Colloidal Anhyhdrous Silica, Talcum Powder

Questions?

Call 1-866-964-0939